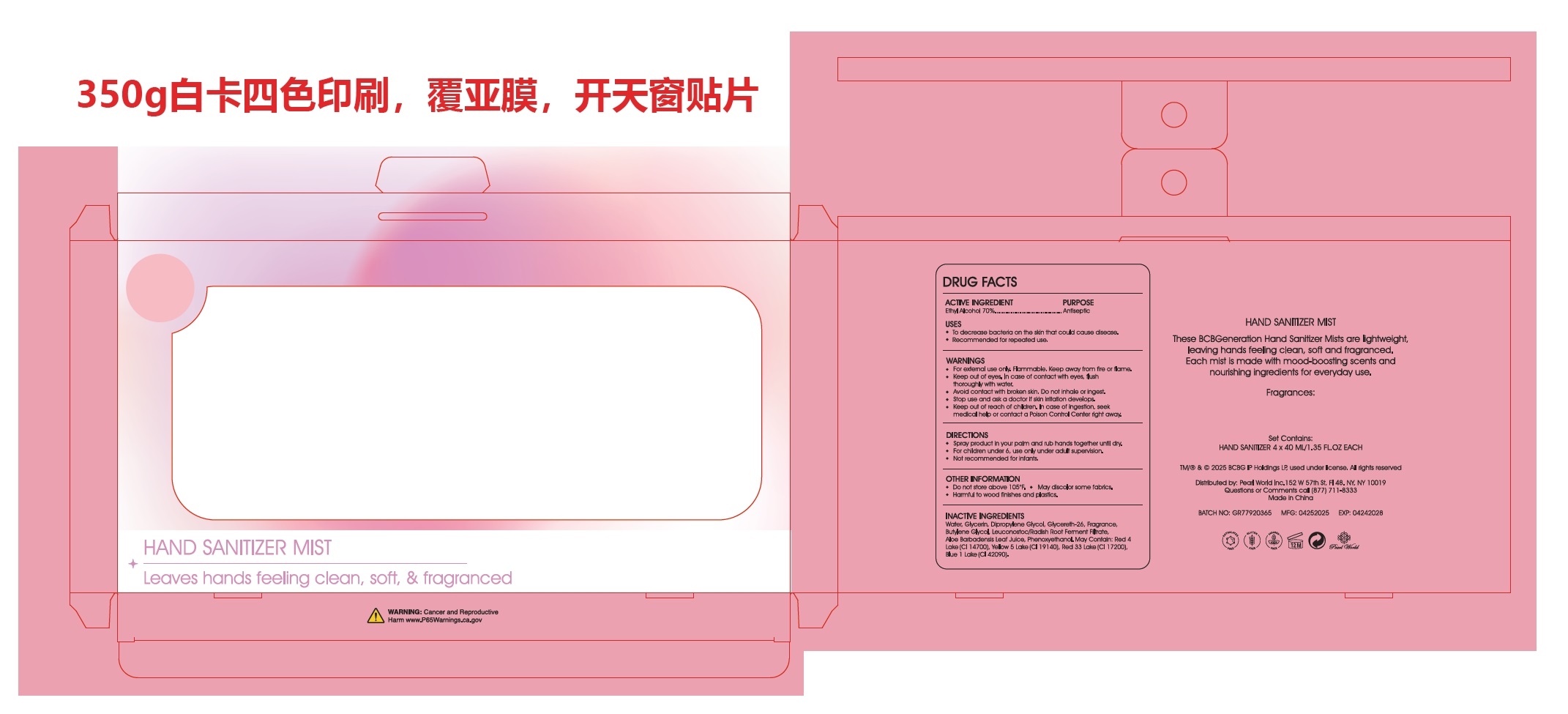 DRUG LABEL: Hand Sanitizer Mist
NDC: 85472-002 | Form: SPRAY
Manufacturer: ZHEJIANG GAORONG COSMETIC CO.,LTD.
Category: otc | Type: HUMAN OTC DRUG LABEL
Date: 20250412

ACTIVE INGREDIENTS: ALCOHOL 71 mL/100 mL
INACTIVE INGREDIENTS: WATER; GLYCERETH-26; BUTYLENE GLYCOL; D&C RED NO. 33; DIPROPYLENE GLYCOL; FD&C RED NO. 4; FD&C BLUE NO. 1; LEUCONOSTOC/RADISH ROOT FERMENT FILTRATE; ALOE BARBADENSIS LEAF JUICE; GLYCERIN; PHENOXYETHANOL; FD&C YELLOW NO. 5; FD&C RED NO. 40

Active ingredient

ETHYL ALCOHOL 70%

USE

To decrease bacteria on the skin that could cause disease.
Recommended for repeated use.

Warning

For external use only. Flammable. keep away from fire or flame

Keep out of eyes, in case of contact with eyes, flush

thoroughly with water.

Avoid contact with broken skin. Do not inhale or ingest.

Stop use and ask a doctor if skin irritation develops.

Keep out of reach of children.In case of ingestion, seek

medical help or contact a Poison Control Center right away.

WHEN USING

none

Stop use and ask a doctor if skin irritation develops.

Keep out of reach of children. In case of ingestion, seek
medical help or contact a Poison Control Center right away.

Purpose

ANTISEPTIC

Other information

Do not store above 105'F,

May discolor some fabrics
Harmful to wood finishes and plastics,

Directions

Spary product in your palm and rub hands together until dry.

For children under 6, use only under adult supervision

Not recommended for infants

Inactive Ingredients

Water, Glycerin, Dipropylene Glycol, Glycereth-26,Fragrance, Butylene Glycol, Leuconostoc Radish RootFerment Filtrate, Aloe Barbadensis Leaf Juice,Phenoxyethanol. May Contain: Red 4 Lake(Cl 14700),Yellow 5 Lake(Cl19140),Red 33 Lake(C117200),Blue 1(Cl 42090)